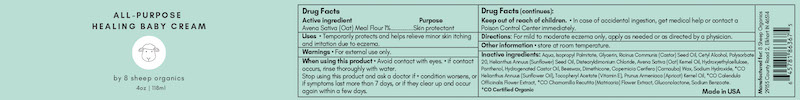 DRUG LABEL: All Purpose Healing Baby Cream
NDC: 68062-3301 | Form: CREAM
Manufacturer: Spa de Soleil
Category: otc | Type: HUMAN OTC DRUG LABEL
Date: 20260120

ACTIVE INGREDIENTS: OATMEAL 1.18 mg/118 mL
INACTIVE INGREDIENTS: POLYSORBATE 20; SODIUM BENZOATE; COPERNICIA CERIFERA (CARNAUBA) WAX; WATER; ISOPROPYL PALMITATE; GLYCERIN; BEESWAX; PRUNUS ARMENIACA (APRICOT) KERNEL EXTRACT; MATRICARIA CHAMOMILLA FLOWERING TOP OIL; RICINUS COMMUNIS (CASTOR) SEED OIL; HYDROXYETHYLCELLULOSE; HYDROGENATED CASTOR OIL; DIMETHICONE; SODIUM HYDROXIDE; HELIANTHUS ANNUUS FLOWERING TOP; .ALPHA.-TOCOPHEROL ACETATE; HELIANTHUS ANNUUS (SUNFLOWER) SEED OIL; CETYL ALCOHOL; DISTEARYLDIMONIUM CHLORIDE; PANTHENOL; GLUCONOLACTONE; CALENDULA OFFICINALIS FLOWERING TOP; AVENA SATIVA (OAT) KERNEL OIL

Skin Relief Cream

Active Ingredient

Oatmeal 1%

Purpose

Skin Protectant

Warnings

For external use only.

When using this product • Avoid contact with eyes. • If contact occurs, rinse thoroughly with water.
Stop using this product and ask a doctor if • condition worsens, or if symptoms last more than 7 days, or if they clear up and occur again within a few days.

Keep out of reach of children. • In case of accidental ingestion, get medical help or contact a Poison Control Center immediately.

Directions

Directions: For mild to moderate eczema on body, apply as needed or as directed by a physician.

Uses:

Uses • Temporarily protects and helps relieve minor skin itching and irritation due to eczema.

Inactive Ingredients:

Inactive ingredients: Aqua, Isopropyl Palmitate, Glycerin, Ricinus Communis (Castor) Seed Oil, Cetyl Alcohol, Polysorbate 20, Helianthus Annuus (Sunflower) Seed Oil, Distearyldimonium Chloride, Avena Sativa (Oat) Kernel Oil, Hydroxyethylcellulose, Panthenol, Hydrogenated Castor Oil, Beeswax, Dimethicone, Copernicia Cerifera (Carnauba) Wax, Sodium Hydroxide, *CO Helianthus Annuus (Sunflower Oil), Tocopheryl Acetate (Vitamin E), Prunus Armeniaca (Apricot) Kernel Oil, *CO Calendula Officinalis Flower Extract, *CO Chamomilla Recutita (Matricaria) Flower Extract, Gluconolactone, Sodium Benzoate.
*CO Certified Organic

Warning

Keep out of reach of children.